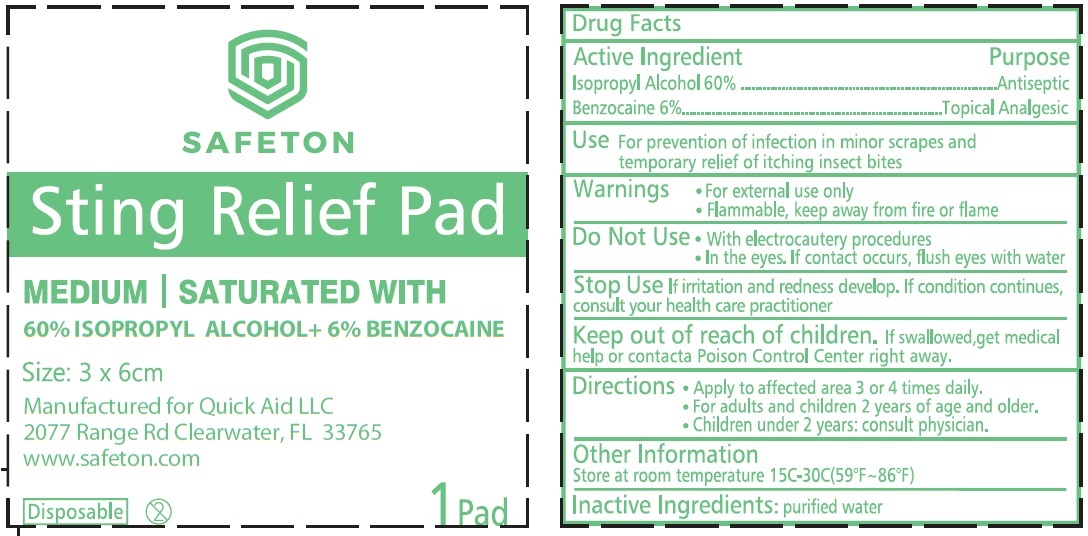 DRUG LABEL: Safeton Sting Relief Pad 60 Isopropyl Alcohol 6 Benzocaine
NDC: 83006-004 | Form: SWAB
Manufacturer: QUICK AID LLC
Category: otc | Type: HUMAN OTC DRUG LABEL
Date: 20221019

ACTIVE INGREDIENTS: ISOPROPYL ALCOHOL 0.6 mL/1 g; BENZOCAINE 60 mg/1 g
INACTIVE INGREDIENTS: WATER

Safeton Sting Relief Pad 60% Isopropyl Alcohol + 6% Benzocaine

Active Ingredient

Isopropyl Alcohol 60%

Benzocaine 6%

Purpose

Antiseptic

Topical Analgesic

Use

For prevention of infection in minor scrapes and temporary relief of itching insect bites

Warnings

- For external use only
- Flammable, keep away from fire or flame

Do Not Use

- With electrocautery procedures
- In the eyes, If contact occurs, flush eyes with water

Stop Use

- if irritation and redness develop. If condition continues, consult your health care practitioner

Keep out of reach of children.

If swallowed, get medical help or contact a Poison Control Center right away.

Directions

- Apply to affected area 3 or 4 times daily.
- For adults and children 2 years of age and older.
- Children under 2 years: consult physician.

Other Information

Store at room temperature 15-30C (59°F~86°F)

Inactive ingredients

purified water